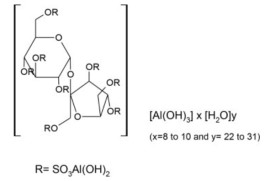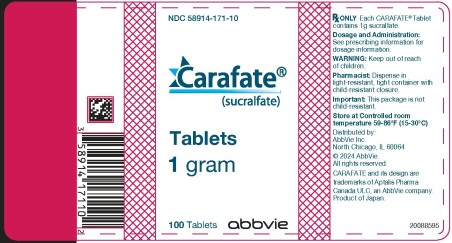 DRUG LABEL: Carafate
NDC: 58914-171 | Form: TABLET
Manufacturer: Allergan, Inc.
Category: prescription | Type: HUMAN PRESCRIPTION DRUG LABEL
Date: 20240521

ACTIVE INGREDIENTS: SUCRALFATE 1 g/1 1
INACTIVE INGREDIENTS: MAGNESIUM STEARATE 12 mg/1 1; CELLULOSE, MICROCRYSTALLINE 115 mg/1 1; D&C RED NO. 30 1.25 mg/1 1; FD&C BLUE NO. 1 0.16 mg/1 1; STARCH, CORN 76.59 mg/1 1

CARAFATE® Tablets
(sucralfate)

DESCRIPTION

CARAFATE Tablets contain sucralfate and sucralfate is an α-D-glucopyranoside, β-D- fructofuranosyl-, octakis-(hydrogen sulfate), aluminum complex.

Tablets for oral administration contain 1 g of sucralfate.

Also contain: D & C Red #30 Lake, FD&C Blue #1 Lake, magnesium stearate, microcrystalline cellulose, and starch. Therapeutic category: antiulcer.

CLINICAL PHARMACOLOGY

Sucralfate is only minimally absorbed from the gastrointestinal tract. The small amounts of the sulfated disaccharide that are absorbed are excreted primarily in the urine.

Although the mechanism of sucralfate’s ability to accelerate healing of duodenal ulcers remains to be fully defined, it is known that it exerts its effect through a local, rather than systemic, action. The following observations also appear pertinent:

1. Studies in human subjects and with animal models of ulcer disease have shown that sucralfate forms an ulcer-adherent complex with proteinaceous exudate at the ulcer site.
2. In vitro, a sucralfate-albumin film provides a barrier to diffusion of hydrogen ions.
3. In human subjects, sucralfate given in doses recommended for ulcer therapy inhibits pepsin activity in gastric juice by 32%.
4. In vitro, sucralfate adsorbs bile salts.

These observations suggest that sucralfate’s antiulcer activity is the result of formation of an ulcer-adherent complex that covers the ulcer site and protects it against further attack by acid, pepsin, and bile salts. There are approximately 14 to 16 mEq of acid-neutralizing capacity per 1 g dose of sucralfate.

CLINICAL TRIALS

Acute Duodenal Ulcer

Over 600 patients have participated in well-controlled clinical trials worldwide. Multicenter trials conducted in the United States, both of them placebo-controlled studies with endoscopic evaluation at 2 and 4 weeks, showed:

STUDY 1
Treatment Groups | Ulcer Healing/ No. Patients
 | 2 wk | 4 wk (Overall)
Sucralfate Placebo | 37/105 (35.2%) 26/106 (24.5%) | 82/109 (75.2%) 68/107 (63.6%)

STUDY 2
Treatment Groups | Ulcer Healing/ No. Patients
 | 2 wk | 4 wk (Overall)
Sucralfate Placebo | 8/24 (33%) 4/31 (13%) | 22/24 (92%) 18/31 (58%)

The sucralfate-placebo differences were statistically significant in both studies at 4 weeks but not at 2 weeks. The poorer result in the first study may have occurred because sucralfate was given 2 hours after meals and at bedtime rather than 1 hour before meals and at bedtime, the regimen used in international studies and in the second United States study. In addition, in the first study liquid antacid was utilized as needed, whereas in the second study antacid tablets were used.

Maintenance Therapy After Healing of Duodenal Ulcer

Two double-blind randomized placebo-controlled U.S. multicenter trials have demonstrated that sucralfate (1 g bid) is effective as maintenance therapy following healing of duodenal ulcers. In one study, endoscopies were performed monthly for 4 months. Of the 254 patients who enrolled, 239 were analyzed in the intention-to-treat life table analysis presented below.

Duodenal Ulcer Recurrence Rate (%)
 | Months of Therapy
Drug | n | 1 | 2 | 3 | 4
CARAFATE Placebo | 122 117 | 20* 33 | 30* 46 | 38† 55 | 42† 63
*P<0.05,†P<0.01

In this study, prn antacids were not permitted.

In the other study, scheduled endoscopies were performed at 6 and 12 months, but for-cause endoscopies were permitted as symptoms dictated. Median symptom scores between the sucralfate and placebo groups were not significantly different. A life table intention-to-treat analysis for the 94 patients enrolled in the trial had the following results:

Duodenal Ulcer Recurrence Rate (%)
Drug | n | 6 months | 12 months
CARAFATE Placebo | 48 46 | 19* 54 | 27* 65

*P<0.002

In this study, prn antacids were permitted.

Data from placebo-controlled studies longer than 1 year are not available.

INDICATIONS AND USAGE

CARAFATE® (sucralfate) is indicated in:

- Short-term treatment (up to 8 weeks) of active duodenal ulcer. While healing with sucralfate may occur during the first week or two, treatment should be continued for 4 to 8 weeks unless healing has been demonstrated by x-ray or endoscopic examination.
- Maintenance therapy for duodenal ulcer patients at reduced dosage after healing of acute ulcers.

CONTRAINDICATIONS

Carafate is contraindicated in patients with known hypersensitivity reactions to the active substance or to any of the excipients.

PRECAUTIONS

The physician should read the “PRECAUTIONS” section when considering the use of this drug in pregnant or pediatric patients, or patients of childbearing potential.

Duodenal ulcer is a chronic, recurrent disease. While short-term treatment with sucralfate can result in complete healing of the ulcer, a successful course of treatment with sucralfate should not be expected to alter the post healing frequency or severity of duodenal ulceration.

Isolated reports of sucralfate tablet aspiration with accompanying respiratory complications have been received. Therefore, sucralfate tablets should be used with caution by patients who have known conditions that may impair swallowing, such as recent or prolonged intubation, tracheostomy, prior history of aspiration, dysphagia, or any other conditions that may alter gag and cough reflexes, or diminish oropharyngeal coordination or motility.

Special Populations: Chronic Renal Failure and Dialysis Patients

When sucralfate is administered orally, small amounts of aluminum are absorbed from the gastrointestinal tract. Concomitant use of sucralfate with other products that contain aluminum, such as aluminum-containing antacids, may increase the total body burden of aluminum.

Patients with normal renal function receiving the recommended doses of sucralfate and aluminum-containing products adequately excrete aluminum in the urine. Patients with chronic renal failure or those receiving dialysis have impaired excretion of absorbed aluminum. In addition, aluminum does not cross dialysis membranes because it is bound to albumin and transferrin plasma proteins. Aluminum accumulation and toxicity (aluminum osteodystrophy, osteomalacia, encephalopathy) have been described in patients with renal impairment. Sucralfate should be used with caution in patients with chronic renal failure.

Drug Interactions

Some studies have shown that simultaneous sucralfate administration in healthy volunteers reduced the extent of absorption (bioavailability) of single doses of the following: cimetidine, digoxin, fluoroquinolone antibiotics, ketoconazole, l-thyroxine, phenytoin, quinidine, ranitidine, tetracycline, and theophylline. Subtherapeutic prothrombin times with concomitant warfarin and sucralfate therapy have been reported in spontaneous and published case reports. However, two clinical studies have demonstrated no change in either serum warfarin concentration or prothrombin time with the addition of sucralfate to chronic warfarin therapy.

The mechanism of these interactions appears to be nonsystemic in nature, presumably resulting from sucralfate binding to the concomitant agent in the gastrointestinal tract. In all case studies to date (cimetidine, ciprofloxacin, digoxin, norfloxacin, ofloxacin, and ranitidine), dosing the concomitant medication 2 hours before sucralfate eliminated the interaction. Because of the potential of CARAFATE to alter the absorption of some drugs, CARAFATE should be administered separately from other drugs when alterations in bioavailability are felt to be critical. In these cases, patients should be monitored appropriately.

Carcinogenesis, Mutagenesis, Impairment of Fertility

Chronic oral toxicity studies of 24 months’ duration were conducted in mice and rats at doses up to 1 g/kg (12 times the human dose).

There was no evidence of drug-related tumorigenicity. A reproduction study in rats at doses up to 38 times the human dose did not reveal any indication of fertility impairment. Mutagenicity studies were not conducted.

Pregnancy

Teratogenic effects

Teratogenicity studies have been performed in mice, rats, and rabbits at doses up to 50 times the human dose and have revealed no evidence of harm to the fetus due to sucralfate. There are, however, no adequate and well-controlled studies in pregnant women. Because animal reproduction studies are not always predictive of human response, this drug should be used during pregnancy only if clearly needed.

Nursing Mothers

It is not known whether this drug is excreted in human milk. Because many drugs are excreted in human milk, caution should be exercised when sucralfate is administered to a nursing woman.

Pediatric Use

Safety and effectiveness in pediatric patients have not been established.

Geriatric Use

Clinical studies of CARAFATE (sucralfate) Tablets did not include sufficient numbers of subjects aged 65 and over to determine whether they respond differently from younger subjects. Other reported clinical experience has not identified differences in responses between the elderly and younger patients. In general, dose selection for an elderly patient should be cautious, usually starting at the low end of the dosing range, reflecting the greater frequency of decreased hepatic, renal, or cardiac function, and of concomitant disease or other drug therapy (See DOSAGE AND ADMINISTRATION).

This drug is known to be substantially excreted by the kidney, and the risk of toxic reactions to this drug may be greater in patients with impaired renal function (See PRECAUTIONS, Special Populations: Chronic Renal Failure and Dialysis Patients). Because elderly patients are more likely to have decreased renal function, care should be taken in dose selection, and it may be useful to monitor renal function.

ADVERSE REACTIONS

Adverse reactions to sucralfate in clinical trials were minor and only rarely led to discontinuation of the drug. In studies involving over 2700 patients treated with sucralfate tablets, adverse effects were reported in 129 (4.7%).

Constipation was the most frequent complaint (2%). Other adverse effects reported in less than 0.5% of the patients are listed below by body system:

Gastrointestinal: diarrhea, nausea, vomiting, gastric discomfort, indigestion, flatulence, dry mouth

Dermatological: pruritus, rash

Nervous System: dizziness, insomnia, sleepiness, vertigo

Other: back pain, headache

Post-marketing: cases of hypersensitivity have been reported with the use of sucralfate tablets, including dyspnea, lip swelling, pruritus, rash, and urticaria.

Cases of anaphylactic reactions, bronchospasm, laryngeal edema, edema of the mouth, Pharyngeal edema, respiratory tract edema and swelling of the face have been reported with an unknown oral formulation of sucralfate.

Bezoars have been reported in patients treated with sucralfate. The majority of patients had underlying medical conditions that may predispose to bezoar formation (such as delayed gastric emptying) or were receiving concomitant enteral tube feedings.

Inadvertent injection of insoluble sucralfate and its insoluble excipients has led to fatal complications, including pulmonary and cerebral emboli. Sucralfate is not intended for intravenous administration.

OVERDOSAGE

Due to limited experience in humans with overdosage of sucralfate, no specific treatment recommendations can be given. Acute oral toxicity studies in animals, however, using doses up to 12 g/kg body weight, could not find a lethal dose. Sucralfate is only minimally absorbed from the gastrointestinal tract. Risks associated with acute overdosage should, therefore, be minimal. In rare reports describing sucralfate overdose, most patients remained asymptomatic. Those few reports where adverse events were described included symptoms of dyspepsia, abdominal pain, nausea, and vomiting.

DOSAGE AND ADMINISTRATION

Active Duodenal Ulcer: The recommended adult oral dosage for duodenal ulcer is 1 g four times per day on an empty stomach.

Antacids may be prescribed as needed for relief of pain but should not be taken within one-half hour before or after sucralfate.

While healing with sucralfate may occur during the first week or two, treatment should be continued for 4 to 8 weeks unless healing has been demonstrated by x-ray or endoscopic examination.

Maintenance Therapy: The recommended adult oral dosage is 1 g twice a day.

Elderly: In general, dose selection for an elderly patient should be cautious, usually starting at the low end of the dosing range, reflecting the greater frequency of decreased hepatic, renal, or cardiac function, and of concomitant disease or other drug therapy (See PRECAUTIONS, Geriatric Use).

Call your doctor for medical advice about side effects. You may report side effects to AbbVie, Inc. at 1-800-678-1605 or FDA at 1-800-FDA-1088 or www.fda.gov/medwatch.

HOW SUPPLIED

CARAFATE (sucralfate) 1 g tablets are supplied in bottles of 100 (NDC 58914-171-10). Light pink, scored, oblong tablets are embossed with CARAFATE on one side and 1712 on the other.

Storage

Store at Controlled room temperature 59-86°F (15-30°C).

Rx Only

Prescribing Information rev. May 2024

Distributed by:
AbbVie, Inc.
North Chicago, IL
60064

© 2024 AbbVie. All rights reserved.

CARAFATE and its design are trademarks of Aptalis Pharma Canada ULC, an AbbVie company.

PRINCIPAL DISPLAY PANEL

NDC 58914-171-10
Carafate®
(sucralfate)
Tablets
1 gram
100 Tablets
abbvie